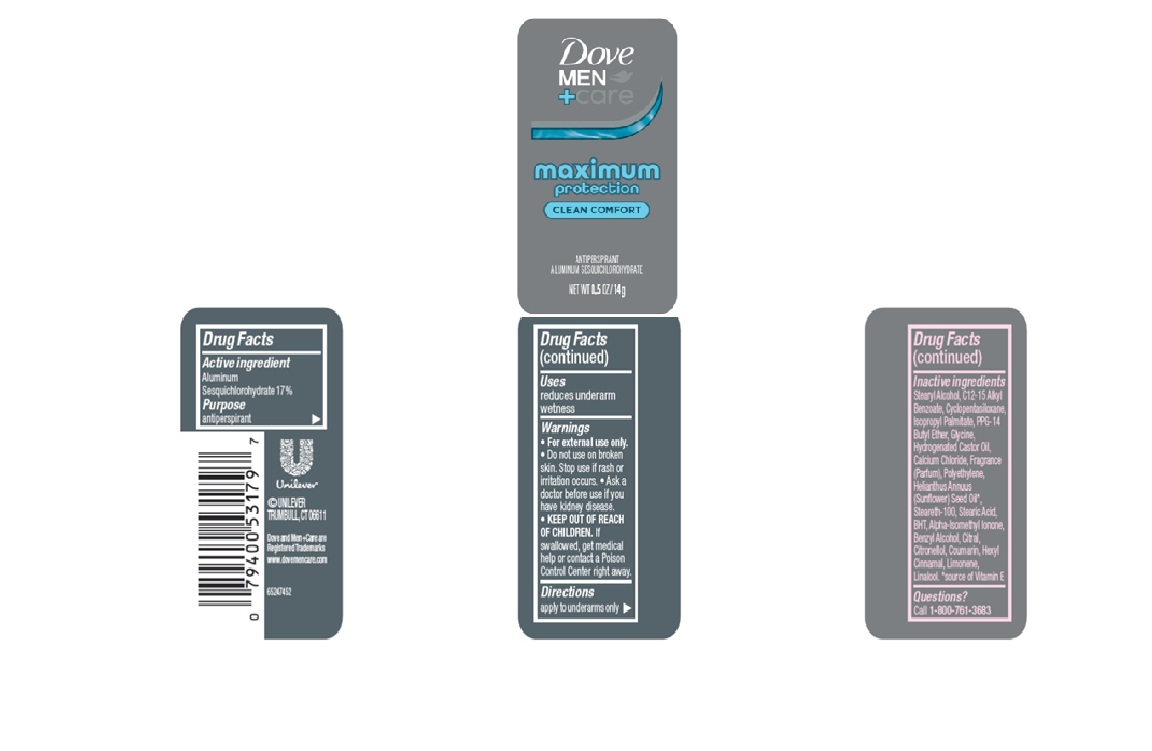 DRUG LABEL: Dove Men Care
NDC: 64942-2412 | Form: STICK
Manufacturer: Conopco d/b/a Unilever
Category: otc | Type: HUMAN OTC DRUG LABEL
Date: 20251209

ACTIVE INGREDIENTS: ALUMINUM SESQUICHLOROHYDRATE 17 g/100 g
INACTIVE INGREDIENTS: HELIANTHUS ANNUUS (SUNFLOWER) SEED OIL; BHT; ISOPROPYL PALMITATE; STEARYL ALCOHOL; POLYETHYLENE; STEARIC ACID; CALCIUM CHLORIDE; C12-15 ALKYL BENZOATE; BENZYL ALCOHOL; COUMARIN; CYCLOPENTASILOXANE; PPG-14 BUTYL ETHER; GLYCINE; HYDROGENATED CASTOR OIL; CITRONELLOL; STEARETH-100; ALPHA-ISOMETHYL IONONE; CITRAL; HEXYL CINNAMAL; LINALOOL; LIMONENE, (+)-

Dove + Men Care Maximum Protection Clean Comfort Antiperspirant Stick

DESCRIPTION

Dove + Men Care Maximum Protection Clean Comfort Antiperspirant Stick

ACTIVE INGREDIENT

Aluminum Sesquichlorohydrate 17%

PURPOSE

Antiperspirant

INDICATIONS AND USAGE

reduces underarm wetness

WARNINGS

• For external use only.
• Do not use on broken skin. Stop use if rash or irritation occurs.• Ask a doctor before use if you have kidney disease. • If swallowed, get medical help or contact a Poison Control Center right away.

• KEEP OUT OF REACH OF CHILDREN.

DOSAGE AND ADMINISTRATION

apply to underarms only

INACTIVE INGREDIENT

Stearyl Alcohol, C12-15 AlkylcBenzoate, Cyclopentasiloxane, Isopropyl Palmitate, PPG-14 Butyl Ether, Glycine, Hydrogenated Castor Oil, Calcium Chloride, Fragrance (Parfum), Polyethylene, Helianthus Annuus (Sunflower) Seed Oil, Steareth-100, Stearic Acid, BHT, Alpha-Isomethyl Ionone, Benzyl Alcohol, Citral, Citronellol, Coumarin, Hexyl Cinnamal, Limonene, Linalool.

QUESTIONS

Call 1-800-761-3683